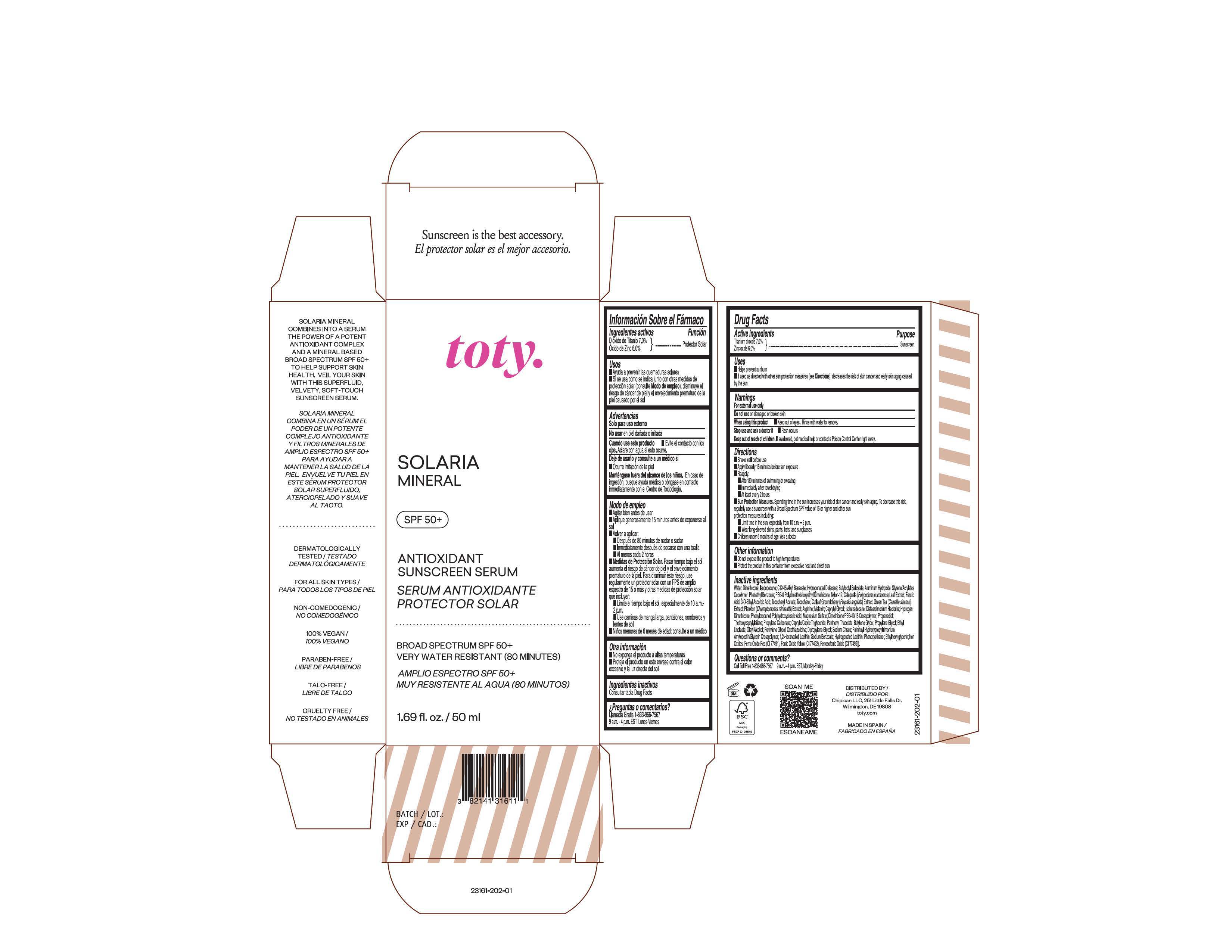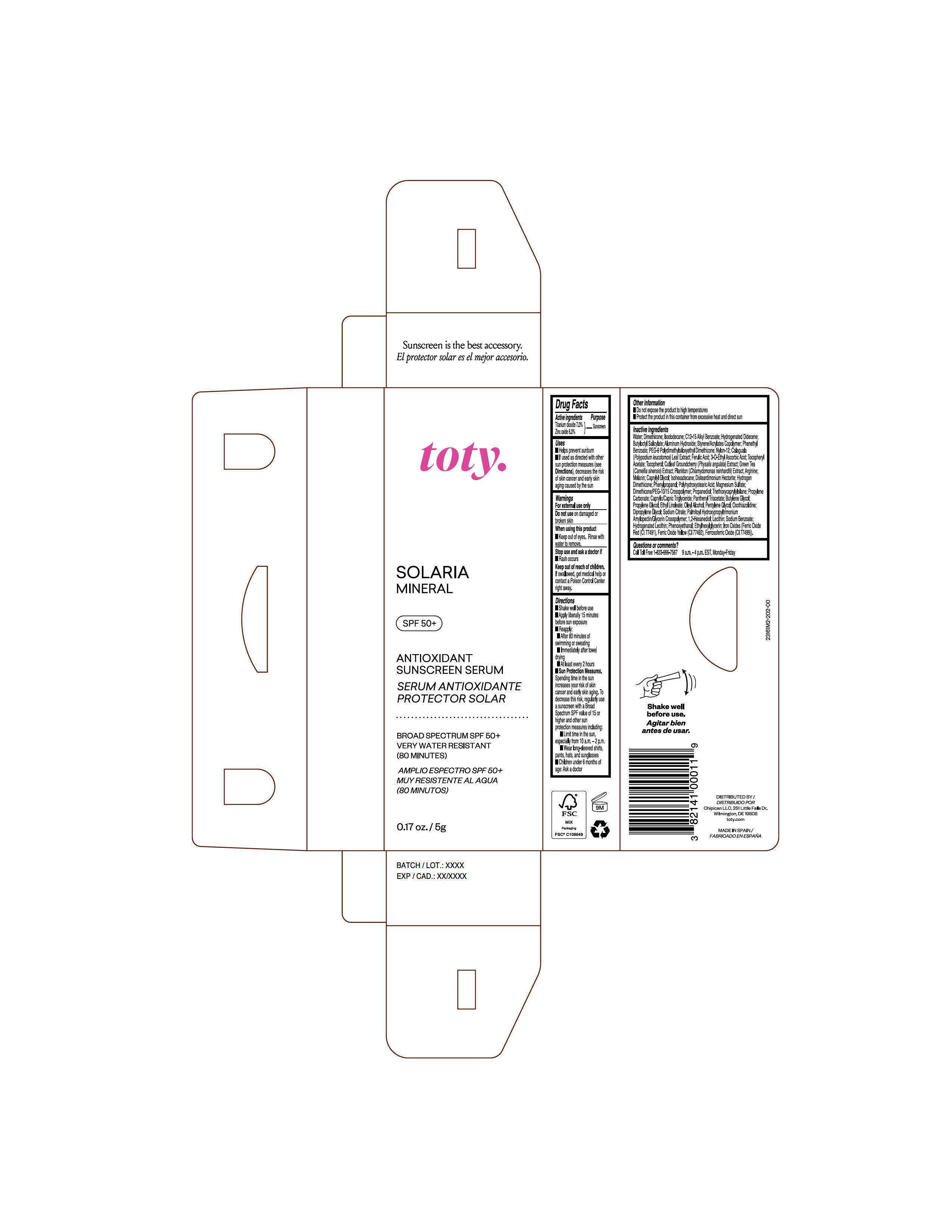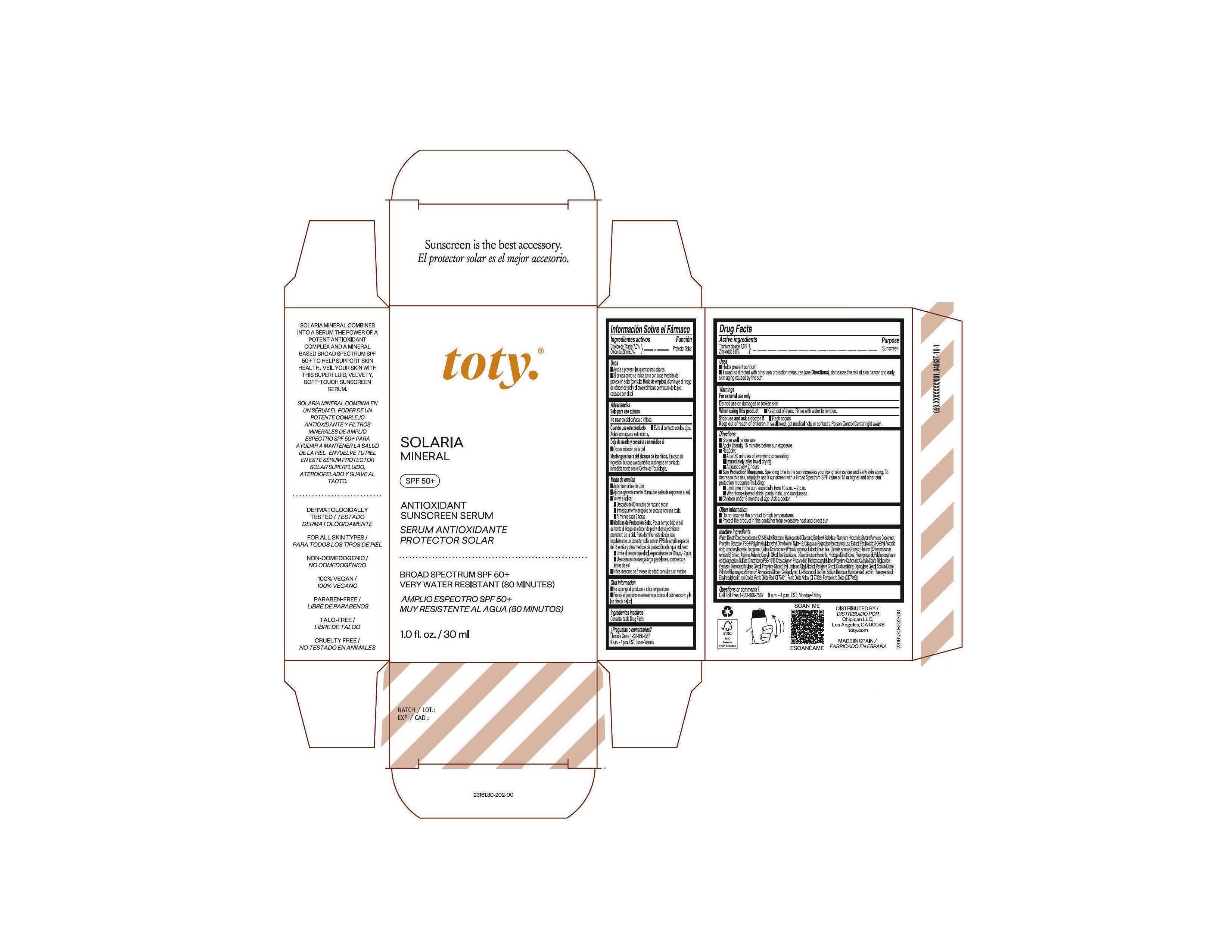 DRUG LABEL: toty Solaria Mineral
NDC: 82141-3161 | Form: CREAM
Manufacturer: Chipican LLC
Category: otc | Type: HUMAN OTC DRUG LABEL
Date: 20240201

ACTIVE INGREDIENTS: TITANIUM DIOXIDE 7 g/100 g; ZINC OXIDE 6 g/100 g
INACTIVE INGREDIENTS: PEG-9 POLYDIMETHYLSILOXYETHYL DIMETHICONE; ISOHEXADECANE; POLYHYDROXYSTEARIC ACID STEARATE; TRIETHOXYCAPRYLYLSILANE; OXOTHIAZOLIDINE; FERRIC OXIDE RED; NYLON-12; ETHYLHEXYLGLYCERIN; 3-PHENYL-1-PROPANOL; HYDROGENATED DIDECENE; BUTYLOCTYL SALICYLATE; PHENETHYL BENZOATE; TOCOPHEROL; PHYSALIS ANGULATA; PROPANEDIOL; LECITHIN, SOYBEAN; HYDROGENATED SOYBEAN LECITHIN; PHLEBODIUM AUREUM LEAF; DIMETHICONE/PEG-10/15 CROSSPOLYMER; FERRIC OXIDE YELLOW; ETHYL LINOLEATE; OLEYL ALCOHOL; GREEN TEA LEAF; BUTYL METHACRYLATE/METHYL METHACRYLATE/METHACRYLIC ACID/STYRENE CROSSPOLYMER; 1,2-HEXANEDIOL; ALUMINUM HYDROXIDE; WATER; ISODODECANE; ARGININE; .ALPHA.-TOCOPHEROL ACETATE; FERULIC ACID; CAPRYLYL GLYCOL; PROPYLENE CARBONATE; PHENOXYETHANOL; PROPYLENE GLYCOL; FERROSOFERRIC OXIDE; ALKYL (C12-15) BENZOATE; BUTYLENE GLYCOL; PENTYLENE GLYCOL; DIPROPYLENE GLYCOL; 3-O-ETHYL ASCORBIC ACID; SODIUM BENZOATE; MAGNESIUM SULFATE HEPTAHYDRATE; HYDROGEN DIMETHICONE (20 CST); ANHYDROUS TRISODIUM CITRATE; DISTEARDIMONIUM HECTORITE; MEDIUM-CHAIN TRIGLYCERIDES; PANTHENOL TRIACETATE, (+)-; CHLAMYDOMONAS REINHARDTII; MELANIN SYNTHETIC (TYROSINE, PEROXIDE); DIMETHICONE; PALMITOYL HYDROXYPROPYLTRIMONIUM AMYLOPECTIN/GLYCERIN CROSSPOLYMER

toty Solaria Mineral

Active Ingredients

Titanium Dioxide 7.0%

Zinc Oxide 6.0%

Purpose

Sunscreen

Uses

- Helps prevent sunburn
- If used as directed with other sun protection measures (see Directions), decreases the risk of skin cancer and early skin aging caused by the sun

Warnings

For external use only

Do not use On damaged or broken skin

When using this product Keep out of eyes. Rinse with water to remove.

Stop use and ask a doctor if Rash occurs

Keep out of reach of children. If swallowed, get medical help or contact a Poison Control Center right away.

Directions

- Shake well before use
- Apply liberally 15 minutes before sun exposure
- Reapply:

After 80 minutes of swimming or sweating

Immediately after towel drying

At least every 2 hours

- Sun Protection Measures. Spending time in the sun increases your risk of skin cancer and early skin aging. To decrease this risk, regularly use a sunscreen with a Broad Spectrum SPF value of 15 or higher and other sun protection measures including:

Limit time in the sun, especially from 10 a.m. - 2 p.m.
Wear long-sleeved shirts, pants, hats, and sunglasses

- Children under 6 months of age: Ask a doctor

Other information

- Do not expose the product to high temperatures
- Protect the product in this container from excessive heat and direct sun

Inactive Ingredients

Water, Dimethicone, Isododecane, C12-15 Alkyl Benzoate, Hydrogenated Didecene, Butyloctyl Salicylate, Aluminum Hydroxide, Styrene/Acrylates Copolymer, Phenethyl Benzoate, PEG-9 Polydimethylsiloxyethyl Dimethicone, Nylon-12, Calaguala (Polypodium leucotomos) Leaf Extract, Ferulic Acid, 3-O-Ethyl Ascorbic Acid, Tocopheryl Acetate, Tocopherol, Cutleaf Grouncherry (Physalis angulata) Extract, Green Tea (Camellia sinensis) Extract, Plankton (Chlamydomonas reinhardti) Extract, Arginine, Melanin, Caprylyl Glycol, Isohexadecane, Disteardimonium Hectorite, Hydrogen Dimethicone, Phenylpropanol, Polyhydroxystearic Acid, Magnesium Sulfate, Dimethicone/PEG-10/15 Crosspolymer, Propanediol, Triethoxycaprylylsilane, Propylene Carbonate, Caprylic/Capric Triglyceride, Panthenyl Triacetate, Butylene Glycol, Propylene Glycol, Ethyl Linoleate, Oleyl Alcohol, Pentylene Glycol, Oxothiazolidine, Dipropylene Glycol, Sodium Citrate, Palmitoyl Hydroxypropyltrimonium Amylopectin/Glycerin Crosspolymer, 1,2-Hexanediol, Lecithin, Sodium Benzoate, Hydrogenated Lecithin, Phenoxyethanol, Ethylhexylglycerin, Iron Oxides (Ferric Oxide Red (CI 77491), Ferric Oxide Yellow (CI 77491), Ferrosoferric Oxide (CI 77499)).

Package Label.Principal Display Panel- Sample

NDC 82141-3161-2 (toty Solaria Mineral, Sample)

toty.

SOLARIA

MINERAL

SPF 50+

ANTIOXIDANT

SUNSCREEN SERUM

SERUM ANTIOXIDANTE

PROTECTOR SOLAR

.....................................................................................

BROAD SPECTRUM SPF 50+

VERY WATER RESISTANT

(80 MINUTES)

AMPLIO ESPECTRO SPF 50+

MUY RESISTENTE AL AGUA

(80 MINUTOS)

0.17 oz/5g

Package Label.Principal Display Panel

NDC 82141-3161-1 (toty Solaria Mineral)

toty.

SOLARIA

MINERAL

SPF 50+

ANTIOXIDANT

SUNSCREEN SERUM

SERUM ANTIOXIDANTE

PROTECTOR SOLAR

.....................................................................................

BROAD SPECTRUM SPF 50+

VERY WATER RESISTANT (80 MINUTES)

AMPLIO ESPECTRO SPF 50+

MUY RESISTENTE AL AGUA (80 MINUTOS)

1.69 fl. oz/50 mL

Package Label. Princip[al Display Panel- Travel Size)

NDC 82141-3161-3 (toty Solaria Mineral, Travel Size)

toty.

SOLARIA

MINERAL

SPF 50+

ANTIOXIDANT

SUNSCREEN SERUM

SERUM ANTIOXIDANTE

PROTECTOR SOLAR

.....................................................................................

BROAD SPECTRUM SPF 50+

VERY WATER RESISTANT (80 MINUTES)

AMPLIO ESPECTRO SPF 50+

MUY RESISTENTE AL AGUA (80 MINUTOS)

1.0 fl. oz/30 mL